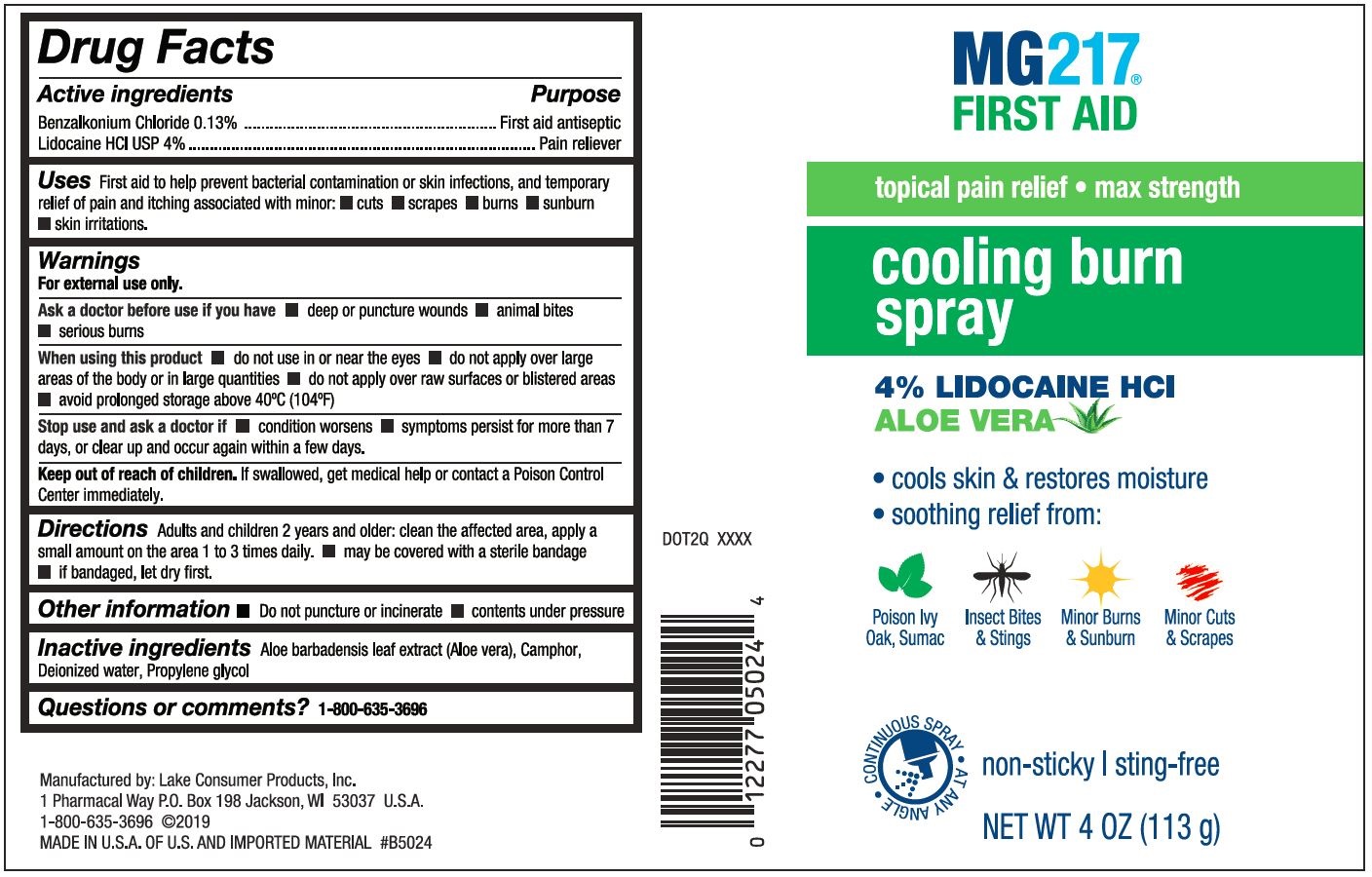 DRUG LABEL: MG217CoolingBurnSpray
NDC: 68093-7319 | Form: SPRAY
Manufacturer: Wisconsin Pharmacal Company
Category: otc | Type: HUMAN OTC DRUG LABEL
Date: 20220113

ACTIVE INGREDIENTS: BENZALKONIUM CHLORIDE 0.013 g/1 g; LIDOCAINE 0.04 g/1 g
INACTIVE INGREDIENTS: PROPYLENE GLYCOL; ALOE VERA LEAF; WATER; CAMPHOR (SYNTHETIC)

MG217 Cooling Burn Spray

PURPOSE

First aid to help prevent bacterial contamination or skin infections, and temporary relief of pain and itching associated with minor: cuts, scrapes, burns, sunburn, skin irritations.

Drug Facts

Active ingredients

Active ingredients | Purpose
Benzalkonium Chloride 0.13% | First aid antiseptic
Lidocaine HCI USP 4% | Pain reliever

Uses

First aid to help prevent bacterial contamination or skin infections, and temporary relief of pain and itching associated with minor: cuts, scrapes, burns, sunburn, skin irritations.

Warnings

For external use only.

Ask a doctor before use if you have • deep puncture wounds • animal bites • serious burns

When using this product • do not use in or near the eyes • do not apply over large areas of the body or in large quantities • do not apply over raw surfaces or blistered areas • avoid prolonged storage above 40C° (104°F)

Stop use and ask a doctor if • condition worsens • symptoms persist for more than 7 days, or clear up and occur again within a few days.

Keep out of reach of children. if swallowed, get medical help or contact a Poison Control Center immediately.

Directions

Adults and children 2 years and older: clean the affected area, apply a small amount on the area 1 to 3 times daily. • may be covered with a sterile bandage • if bandaged, let dry first.

Other information

• Do not puncture or incinerate • contents under pressure

Inactive ingredients

Aloe barbadensis leaf extract (Aloe vera), Camphor, Deionized water, Propylene glycol

Questions or comments?

1-800-635-3696